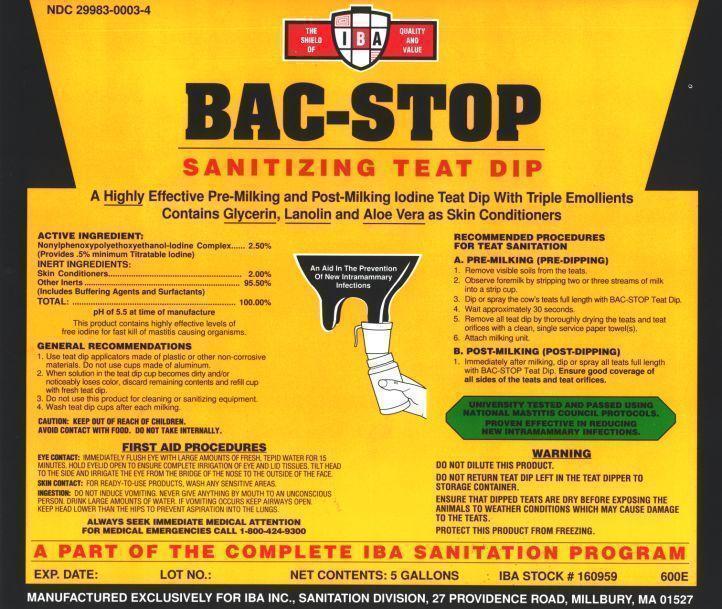 DRUG LABEL: BACSTOP
NDC: 29983-0003 | Form: SOLUTION
Manufacturer: IBA
Category: animal | Type: OTC ANIMAL DRUG LABEL
Date: 20241231

ACTIVE INGREDIENTS: IODINE 5 g/1 L
INACTIVE INGREDIENTS: NONOXYNOL-30; NONOXYNOL-9; CITRIC ACID MONOHYDRATE; GLYCERIN; SODIUM HYDROXIDE; POTASSIUM IODIDE; WATER

BAC-STOP SANITIZING TEAT DIP A HIGHLY EFFECTIVE PRE-MILKING AND POST-MILKING IODINE TEAT DIP WITH TRIPLE EMOLLIENTS CONTAINS GLYCERIN, LANOLIN AND ALOE VERA AS SKIN CONDITIONERS

ACTIVE INGREDIENT:

Nonylphenoxypolyethoxyethanol Iodine Complex.....2.50%
(Provides .5% minimum Titratable Iodine)
INERT INGREDIENTS
Skin Conditioners.............2.00%
Other Inerts.....95.50%
(Includes Buffering Agents and Surfactants)
Total.................100%
pH of 5.5 at time of manufacture

INDICATIONS AND USAGE PROVIDES

GENERAL RECOMMENDATIONS
1. Use teat dip applicators made of plastic or other non-corrosive materials. Do not use cups made of aluminum.
2. When solution in the teat dip cup becomes dirty and/or noticeably loses color, discard remaining contents and refill cup with fresh teat dip.
3. Do not use this product for cleaning or sanitizing equipment.
4. Wash Teat Dip cups after each milking.
RECOMMENDED PROCEDURES FOR TEAT SANITATION
A. PRE-MILKING (PRE-DIPPING)
1. REMOVE VISIBLE SOILS FROM THE TEATS.
2. OBSERVE FOREMILK BY STRIPPING TWO OR THREE STREAMS OF MILK INTO A STRIP CUP.
3. DIP OR SPRAY THE COW'S TEATS FULL LENGTH WITH BAC-STOP TEAT DIP.
4 WAIT APPROXIMATELY 30 SECONDS.
5. REMOVE ALL TEAT DIP BY THOROUGHLY DRYING THE TEATS AND TEAT ORIFICES WITH A CLEAN, SINGLE SERVICE PAPER TOWEL(S).
6. ATTACH MILKING UNIT.
B. POST-MILKING (POST -DIPPING)
Immediately after milking, dip or spray all teats full length with BAC-STOP Teat Dip. Ensure good coverage of all sides of the teats and teat orifices.

UNIVERSITY TESTED AND PASSED USING NATIONAL MASTITIS COUNCIL PROTOCOLS.

Ã‚Â Ã‚Â Ã‚Â Ã‚Â Ã‚Â Ã‚Â Ã‚Â PROVEN EFFECTIVE IN REDUCING NEW INTRAMAMMARY INFECTIONS.

PART OF THE COMPLETE IBA SANITATION PROGRAM

WARNING

DO NOT DILUTE THIS PRODUCT.
DO NOT RETURN TEAT DIP LEFT IN THE TEAT DIPPER TO STORAGE CONTAINER
ENSURE THAT DIPPED TEATS ARE DRY BEFORE EXPOSING THE ANIMALS TO WEATHER CONDITIONS WHICH MAY CAUSE DAMAGE TO THE TEATS.
PROTECT THIS PRODUCT FROM FREEZING.
CAUTION: KEEP OUT OF REACH OF CHILDREN.
AVOID CONTACT WITH FOOD. DO NOT TAKE INTERNALLY.

FIRST AID PROCEDURES

EYE CONTACT: IMMEDIATELY FLUSH EYE WITH LARGE AMOUNTS OF FRESH, TEPID WATER FOR 15 MINUTES. HOLD EYELID OPEN TO ENSURE COMPLETE IRRIGATION OF EYE AND LID TISSUES . TILT HEAD TO THE SIDE AND IRRIGATE THE EYE FROM THE BRIDGE OF THE NOSE TO THE OUTSIDE OF THE FACE.

SKIN CONTACT: FOR CONTACT WITH CONCENTRATED PRODUCTS, FLUSH THOROUGHLY WITH FRESH,TEPID WATER, DISCARD CONTAMINATED CLOTHING AND FOOTWEAR OR WASH BEFORE REUSE. FOR READY-TO-USE PRODUCTS, WASH ANY SENSITIVE AREAS.

INGESTION: DO NOT INDUCE VOMITING. NEVER GIVE ANYTHING BY MOUTH TO AN UNCONSCIOUS PERSON. DRINK LARGE AMOUNTS OF WATER. IF VOMITING OCCURS KEEP AIRWAYS OPEN. KEEP HEAD LOWER THAN THE HIPS TO PREVENT ASPIRATION INTO THE LUNGS.

ALWAYS SEEK IMMEDIATE MEDICAL ATTENTION

FOR MEDICAL EMERGENCIES CALL 1-800-424-9300